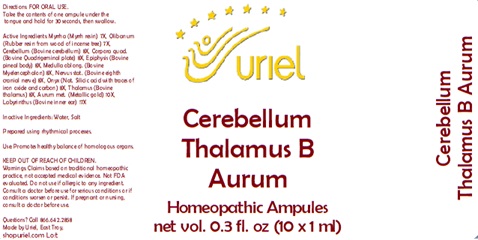 DRUG LABEL: Cerebellum Thalamus B Aurum
NDC: 48951-3277 | Form: LIQUID
Manufacturer: Uriel Pharmacy Inc.
Category: homeopathic | Type: HUMAN OTC DRUG LABEL
Date: 20241216

ACTIVE INGREDIENTS: MYRRH 7 [hp_X]/1 mL; FRANKINCENSE 7 [hp_X]/1 mL; BOS TAURUS CEREBELLUM 8 [hp_X]/1 mL; BOS TAURUS BRAIN 8 [hp_X]/1 mL; BOS TAURUS PINEAL GLAND 8 [hp_X]/1 mL; BOS TAURUS NERVE 8 [hp_X]/1 mL; BIFENTHRIN 8 [hp_X]/1 mL; SUS SCROFA THALAMUS 8 [hp_X]/1 mL; GOLD 10 [hp_X]/1 mL; SUS SCROFA EAR 17 [hp_X]/1 mL
INACTIVE INGREDIENTS: WATER; SODIUM CHLORIDE

Cerebellum Thalamus B Aurum

INDICATIONS AND USAGE

Directions: FOR ORAL USE.

DOSAGE AND ADMINISTRATION

Take the contents of one ampule under the tongue and hold for 30 seconds, then swallow.

ACTIVE INGREDIENT

Active Ingredients: Myrrha (Myrrh resin) 7X, Olibanum (Rubber resin from wood of incense tree) 7X, Cerebellum (Bovine cerebellum) 8X, Corpora quad. (Bovine Quadrigeminal plate) 8X, Epiphysis (Bovine pineal body) 8X, Medulla oblong. (Bovine Myelencephalon) 8X, Nervus stat. (Bovine eighth cranial nerve) 8X, Onyx (Nat. Silicic acid with traces of iron oxide and carbon) 8X, Thalamus (Bovine thalamus) 8X, Aurum met. (Metallic gold) 10X, Labyrinthus (Bovine inner ear) 17X

Inactive Ingredients: Water, Salt

Prepared using rhythmical processes.

PURPOSE

Use: Promotes healthy balance of homologous organs.

KEEP OUT OF REACH OF CHILDREN.

WARNINGS

Warnings: Claims based on traditional homeopathic practice, not accepted medical evidence. Not FDA evaluated. Do not use if allergic to any ingredient. Consult a doctor before use for serious conditions or if conditions worsen or persist. If pregnant or nursing, consult a doctor before use.

QUESTIONS

Questions? Call 866.642.2858 Made by Uriel, East Troy, WI 53120 shopuriel.com Lot: